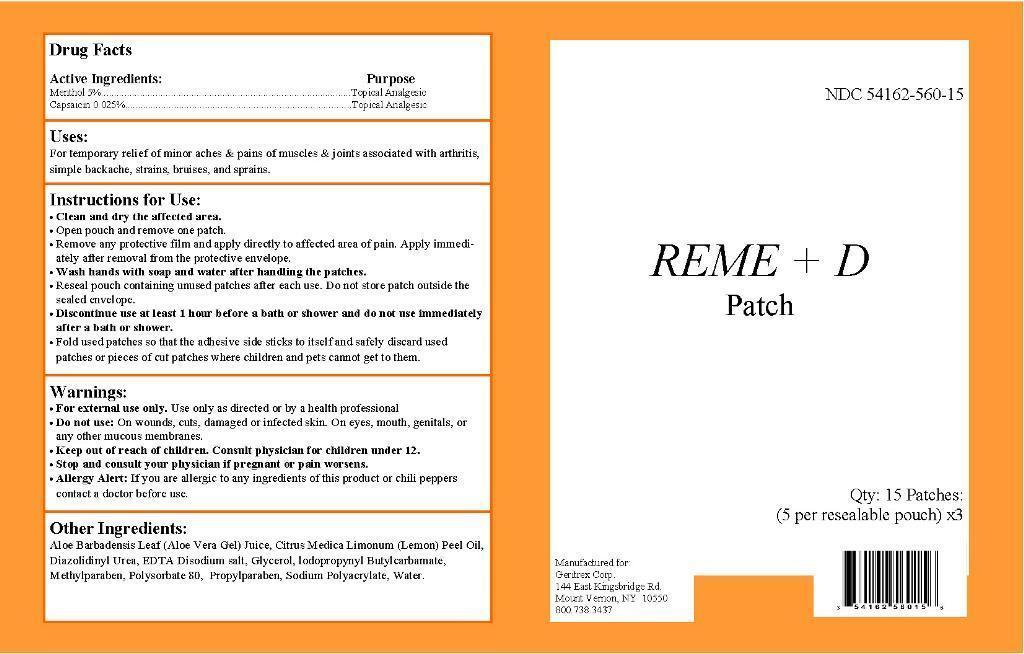 DRUG LABEL: REME D
NDC: 54162-560 | Form: PATCH
Manufacturer: Geritrex Corp
Category: otc | Type: HUMAN OTC DRUG LABEL
Date: 20150220

ACTIVE INGREDIENTS: MENTHOL 5.0 g/100 g; CAPSAICIN 0.025 g/100 g
INACTIVE INGREDIENTS: ALOE VERA LEAF; DIAZOLIDINYL UREA; GLYCERIN; IODOPROPYNYL BUTYLCARBAMATE; LEMON OIL; METHYLPARABEN; POLYSORBATE 80; PROPYLPARABEN; SODIUM POLYACRYLATE (8000 MW); WATER

REME + D Patch

Drug Facts

Active Ingredients Purpose

Menthol 5% Topical Analgesic

Capsaicin 0.025% Topical Analgesic

Uses

For temporary relief of minor aches & pains of muscles & joints associated with arthritis, simple backache, strains, bruises, and sprains.

Instructions for use

Clean and dry the affected area.

Open pouch and remove one patch.

Remove any protective film and apply directly to affected area of pain. Apply immedi-ately after removal from the protective envelope.

Wash hands with soap and water after handling the patches.

Reseal pouch containing unused patches after each use. Do not store patch outside the sealed envelope.

Discontinue use at least 1 hour before a bath or shower and do not use immediately after a bath or shower.

Fold used patches so that the adhesive side sticks to itself and safely discard used patches or pieces of cut patches where children and pets cannot get to them

Warnings

For external use only.

Use only as directed or by a health professional

Do not use: On wounds, cuts, damaged or infected skin. On eyes, mouth, genitals, or any other mucous membranes.

Stop and consult your physician if pregnant or pain worsens.

Allergy Alert: If you are allergic to any ingredients of this product or chili peppers contact a doctor before use

Keep out of reach of children. Consult physician for children under 12.

Storage Condition 15°-30°C (59°-86°F)

DOSAGE AND ADMINISTRATION

Discontinue use at least 1 hour befor a bath or shower and do not use immediately after a bath or shower.